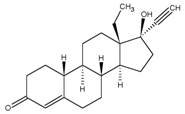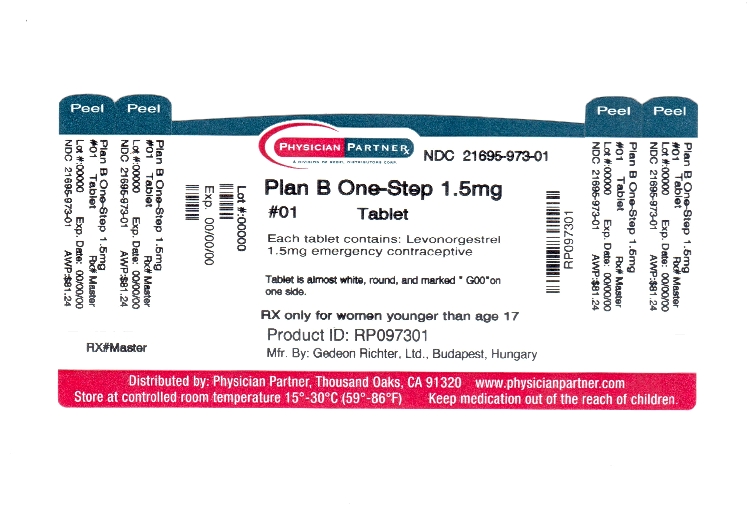 DRUG LABEL: Plan B One-Step
NDC: 21695-973 | Form: TABLET
Manufacturer: Rebel Distributors Corp
Category: prescription | Type: HUMAN PRESCRIPTION DRUG LABEL
Date: 20110913

ACTIVE INGREDIENTS: LEVONORGESTREL 1.5 mg/1 1
INACTIVE INGREDIENTS: SILICON DIOXIDE; STARCH, CORN; LACTOSE MONOHYDRATE; MAGNESIUM STEARATE; STARCH, POTATO; TALC

HIGHLIGHTS OF PRESCRIBING INFORMATION

These highlights do not include all the information needed to use Plan B One-Step safely and effectively. See full prescribing information for Plan B One-Step.
Plan B One-Step (levonorgestrel) tablet, 1.5 mg, for oral use
Initial U.S. Approval: 1982

1 INDICATIONS AND USAGE

Plan B One-Step is a progestin-only emergency contraceptive indicated for prevention of pregnancy following unprotected intercourse or a known or suspected contraceptive failure. Plan B One-Step is available only by prescription for women younger than age 17 years, and available over the counter for women 17 years and older. Plan B One-Step is not intended for routine use as a contraceptive. (1)

2 DOSAGE AND ADMINISTRATION

One tablet taken orally as soon as possible within 72 hours after unprotected intercourse. Efficacy is better if the tablet is taken as soon as possible after unprotected intercourse. (2)

3 DOSAGE FORMS AND STRENGTHS

1.5 mg tablet (3)

4 CONTRAINDICATIONS

Known or suspected pregnancy (4)

5 WARNINGS AND PRECAUTIONS

- Ectopic pregnancy: Women who become pregnant or complain of lower abdominal pain after taking Plan B One- Step should be evaluated for ectopic pregnancy. (5.1)
- Plan B One-Step is not effective in terminating an existing pregnancy. (5.2)
- Effect on menses: Plan B One-Step may alter the next expected menses. If menses is delayed beyond 1 week, pregnancy should be considered. (5.3)
- STI/HIV: Plan B One-Step does not protect against STI/HIV. (5.4)

6 ADVERSE REACTIONS

The most common adverse reactions (≥10%) in clinical trials included heavier menstrual bleeding (31%), nausea (14%), lower abdominal pain (13%), fatigue (13%), headache (10%), and dizziness (10%). (6.1)

To report SUSPECTED ADVERSE REACTIONS, contact Barr Laboratories at 1-800-330-1271 or FDA at 1-800-FDA-1088 or www.fda.gov/medwatch

7 DRUG INTERACTIONS

Drugs or herbal products that induce certain enzymes, such as CYP3A4, may decrease the effectiveness of progestin-only pills. (7)

8 USE IN SPECIFIC POPULATIONS

- Nursing Mothers: Small amounts of progestin pass into the breast milk of nursing women taking progestin-only pills for long-term contraception, resulting in detectable steroid levels in infant plasma. (8.3)
- Plan B One-Step is not intended for use in premenarcheal (8.4) or postmenopausal females (8.5).

FULL PRESCRIBING INFORMATION

1 INDICATIONS AND USAGE

Plan B® One-Step is a progestin-only emergency contraceptive indicated for prevention of pregnancy following unprotected intercourse or a known or suspected contraceptive failure. To obtain optimal efficacy, the tablet should be taken as soon as possible within 72 hours of intercourse.

Plan B One-Step is available only by prescription for women younger than age 17 years, and available over the counter for women 17 years and older.

Plan B One-Step is not indicated for routine use as a contraceptive.

2 DOSAGE AND ADMINISTRATION

Take Plan B One-Step orally as soon as possible within 72 hours after unprotected intercourse or a known or suspected contraceptive failure. Efficacy is better if the tablet is taken as soon as possible after unprotected intercourse. Plan B One-Step can be used at any time during the menstrual cycle.

If vomiting occurs within two hours of taking the tablet, consideration should be given to repeating the dose.

3 DOSAGE FORMS AND STRENGTHS

The Plan B One-Step tablet is supplied as an almost white, round tablet containing 1.5 mg of levonorgestrel and is marked G00 on one side.

4 CONTRAINDICATIONS

Plan B One-Step is contraindicated for use in the case of known or suspected pregnancy.

5 WARNINGS AND PRECAUTIONS

5.1 Ectopic Pregnancy

Ectopic pregnancies account for approximately 2% of all reported pregnancies. Up to 10% of pregnancies reported in clinical studies of routine use of progestin-only contraceptives are ectopic.

A history of ectopic pregnancy is not a contraindication to use of this emergency contraceptive method. Healthcare providers, however, should consider the possibility of an ectopic pregnancy in women who become pregnant or complain of lower abdominal pain after taking Plan B One-Step. A follow-up physical or pelvic examination is recommended if there is any doubt concerning the general health or pregnancy status of any woman after taking Plan B One-Step.

5.2 Existing Pregnancy

Plan B One-Step is not effective in terminating an existing pregnancy.

5.3 Effects on Menses

Some women may experience spotting a few days after taking Plan B One-Step. Menstrual bleeding patterns are often irregular among women using progestin-only oral contraceptives and women using levonorgestrel for postcoital and emergency contraception.

If there is a delay in the onset of expected menses beyond 1 week, consider the possibility of pregnancy.

5.4 STI/HIV

Plan B One-Step does not protect against HIV infection (AIDS) or other sexually transmitted infections (STIs).

5.5 Physical Examination and Follow-up

A physical examination is not required prior to prescribing Plan B One-Step. A follow-up physical or pelvic examination is recommended if there is any doubt concerning the general health or pregnancy status of any woman after taking Plan B One-Step.

5.6 Fertility Following Discontinuation

A rapid return of fertility is likely following treatment with Plan B One-Step for emergency contraception; therefore, routine contraception should be continued or initiated as soon as possible following use of Plan B One-Step to ensure ongoing prevention of pregnancy.

6 ADVERSE REACTIONS

6.1 Clinical Trials Experience

Because clinical trials are conducted under widely varying conditions, adverse reaction rates observed in the clinical trials of a drug cannot be directly compared to rates in the clinical trials of another drug and may not reflect the rates observed in clinical practice.

Plan B One-Step was studied in a randomized, double-blinded multicenter clinical trial. In this study, all women who had received at least one dose of study medication were included in the safety analysis: 1,379 women in the Plan B One-Step group, and 1,377 women in the Plan B group (2 doses of 0.75 mg levonorgestrel taken 12 hours apart). The mean age of women given Plan B One-Step was 27 years. The racial demographic of those enrolled was 54% Chinese, 12% Other Asian or Black, and 34% were Caucasian in each treatment group. 1.6% of women in the Plan B One-Step group and 1.4% in Plan B group were lost to follow-up.

The most common adverse events (>10%) in the clinical trial for women receiving Plan B One-Step included heavier menstrual bleeding (30.9%), nausea (13.7%), lower abdominal pain (13.3%), fatigue (13.3%), and headache (10.3%). Table 1 lists those adverse events that were reported in > 4% of Plan B One-Step users.

Table 1. Adverse Events in > 4% of Women, by % Frequency
Most Common Adverse Events; (MedDRA) | Plan B One-Step; N = 1359 (%)
Heavier menstrual bleeding | 30.9
Nausea | 13.7
Lower abdominal pain | 13.3
Fatigue | 13.3
Headache | 10.3
Dizziness | 9.6
Breast tenderness | 8.2
Delay of menses (> 7 days) | 4.5

6.2 Postmarketing Experience

The following adverse reactions have been identified during post-approval use of Plan B (2 doses of 0.75 mg levonorgestrel taken 12 hours apart). Because these reactions are reported voluntarily from a population of uncertain size, it is not always possible to reliably estimate their frequency or establish a causal relationship to drug exposure.

Gastrointestinal Disorders
Abdominal Pain, Nausea, Vomiting

General Disorders and Administration Site Conditions
Fatigue

Nervous System Disorders
Dizziness, Headache

Reproductive System and Breast Disorders
Dysmenorrhea, Irregular Menstruation, Oligomenorrhea, Pelvic Pain

7 DRUG INTERACTIONS

Drugs or herbal products that induce enzymes, including CYP3A4, that metabolize progestins may decrease the plasma concentrations of progestins, and may decrease the effectiveness of progestin-only pills. Some drugs or herbal products that may decrease the effectiveness of progestin-only pills include:

- barbiturates
- bosentan
- carbamazepine
- felbamate
- griseofulvin
- oxcarbazepine
- phenytoin
- rifampin
- St. John’s wort
- topiramate

Significant changes (increase or decrease) in the plasma levels of the progestin have been noted in some cases of co-administration with HIV protease inhibitors or with non-nucleoside reverse transcriptase inhibitors.

Consult the labeling of all concurrently used drugs to obtain further information about interactions with progestin-only pills or the potential for enzyme alterations.

8 USE IN SPECIFIC POPULATIONS

8.1 Pregnancy

Many studies have found no harmful effects on fetal development associated with long-term use of contraceptive doses of oral progestins. The few studies of infant growth and development that have been conducted with progestin-only pills have not demonstrated significant adverse effects.

8.3 Nursing Mothers

In general, no adverse effects of progestin-only pills have been found on breastfeeding performance or on the health, growth, or development of the infant. However, isolated post-marketing cases of decreased milk production have been reported. Small amounts of progestins pass into the breast milk of nursing mothers taking progestin-only pills for long-term contraception, resulting in detectable steroid levels in infant plasma.

8.4 Pediatric Use

Safety and efficacy of progestin-only pills for long-term contraception have been established in women of reproductive age. Safety and efficacy are expected to be the same for postpubertal adolescents less than 17 years and for users 17 years and older. Use of Plan B One-Step emergency contraception before menarche is not indicated.

8.5 Geriatric Use

This product is not intended for use in postmenopausal women.

8.6 Race

No formal studies have evaluated the effect of race. However, clinical trials demonstrated a higher pregnancy rate in Chinese women with both Plan B and the Yuzpe regimen (another form of emergency contraception). There was a non-statistically significant increased rate of pregnancy among Chinese women in the Plan B One-Step trial. The reason for this apparent increase in the pregnancy rate with emergency contraceptives in Chinese women is unknown.

8.7 Hepatic Impairment

No formal studies were conducted to evaluate the effect of hepatic disease on the disposition of Plan B One-Step.

8.8 Renal Impairment

No formal studies were conducted to evaluate the effect of renal disease on the disposition of Plan B One-Step.

9 DRUG ABUSE AND DEPENDENCE

Levonorgestrel is not a controlled substance. There is no information about dependence associated with the use of Plan B One-Step.

10 OVERDOSAGE

There are no data on overdosage of Plan B One-Step, although the common adverse event of nausea and associated vomiting may be anticipated.

11 DESCRIPTION

The Plan B One-Step tablet contains 1.5 mg of a single active steroid ingredient, levonorgestrel [18,19-Dinorpregn-4-en-20-yn-3-one-13-ethyl-17-hydroxy-, (17 α)-(-)-], a totally synthetic progestogen. The inactive ingredients are colloidal silicon dioxide, corn starch, lactose monohydrate, magnesium stearate, potato starch, and talc.

Levonorgestrel has a molecular weight of 312.45, and the following structural and molecular formulas:

C21H28O2

12 CLINICAL PHARMACOLOGY

12.1 Mechanism of Action

Emergency contraceptive pills are not effective if a woman is already pregnant. Plan B One-Step is believed to act as an emergency contraceptive principally by preventing ovulation or fertilization (by altering tubal transport of sperm and/or ova). In addition, it may inhibit implantation (by altering the endometrium). It is not effective once the process of implantation has begun.

12.3 Pharmacokinetics

Absorption

Following a single dose administration of Plan B One-Step in 30 women under fasting conditions, maximum plasma concentrations of levonorgestrel of 19.1 ng/mL were reached at 1.7 hours. See Table 2.

Table 2. Pharmacokinetic Parameter Values Following Single Dose Administration of Plan B One-Step (levonorgestrel) tablet 1.5 mg to 30 Healthy Female Volunteers under Fasting Conditions
 | Mean (± SD)
 | Cmax (ng/mL) | AUCt (ng·hr/mL) [N=29] | AUCinf (ng·hr/mL) | Tmax (hr) [median (range)] | t1/2 (hr)
Levonorgestrel | 19.1; (9.7) | 294.8; (208.8) | 307.5; (218.5) | 1.7; (1.0-4.0) | 27.5; (5.6)
Cmax = maximum concentration
AUCt = area under the drug concentration curve from time 0 to time of last determinable concentration
AUCinf = area under the drug concentration curve from time 0 to infinity
Tmax = time to maximum concentration
t1/2 = elimination half life

Effect of Food: The effect of food on the rate and the extent of levonorgestrel absorption following single oral administration of Plan B One-Step has not been evaluated.

Distribution

The apparent volume of distribution of levonorgestrel is reported to be approximately 1.8 L/kg. It is about 97.5 to 99% protein-bound, principally to sex hormone binding globulin (SHBG) and, to a lesser extent, serum albumin.

Metabolism

Following absorption, levonorgestrel is conjugated at the 17β-OH position to form sulfate conjugates and, to a lesser extent, glucuronide conjugates in plasma. Significant amounts of conjugated and unconjugated 3α, 5β-tetrahydrolevonorgestrel are also present in plasma, along with much smaller amounts of 3α, 5α-tetrahydrolevonorgestrel and 16βhydroxylevonorgestrel. Levonorgestrel and its phase I metabolites are excreted primarily as glucuronide conjugates. Metabolic clearance rates may differ among individuals by several-fold, and this may account in part for the wide variation observed in levonorgestrel concentrations among users.

Excretion

About 45% of levonorgestrel and its metabolites are excreted in the urine and about 32% are excreted in feces, mostly as glucuronide conjugates.

Specific Populations

Pediatric

This product is not intended for use in the premenarcheal population, and pharmacokinetic data are not available for this population.

Geriatric

This product is not intended for use in postmenopausal women, and pharmacokinetic data are not available for this population.

Race

No formal studies have evaluated the effect of race. However, clinical trials demonstrated a higher pregnancy rate in Chinese women with both Plan B and the Yuzpe regimen (another form of emergency contraception). There was a non-statistically significant increased rate of pregnancy among Chinese women in the Plan B One-Step trial. The reason for this apparent increase in the pregnancy rate with emergency contraceptives in Chinese women is unknown [see USE IN SPECIFIC POPULATIONS (8.6)].

Hepatic Impairment

No formal studies were conducted to evaluate the effect of hepatic disease on the disposition of Plan B One-Step.

Renal Impairment

No formal studies were conducted to evaluate the effect of renal disease on the disposition of Plan B One-Step.

Drug-Drug Interactions

No formal drug-drug interaction studies were conducted with Plan B One-Step [see DRUG INTERACTIONS (7)].

13 NONCLINICAL TOXICOLOGY

13.1 Carcinogenesis, Mutagenesis, Impairment of Fertility

Carcinogenicity: There is no evidence of increased risk of cancer with short-term use of progestins. There was no increase in tumorgenicity following administration of levonorgestrel to rats for 2 years at approximately 5 µg/day, to dogs for 7 years at up to 0.125 mg/kg/day, or to rhesus monkeys for 10 years at up to 250 µg/kg/day. In another 7 year dog study, administration of levonorgestrel at 0.5 mg/kg/day did increase the number of mammary adenomas in treated dogs compared to controls. There were no malignancies.

Genotoxicity: Levonorgestrel was not found to be mutagenic or genotoxic in the Ames Assay, in vitro mammalian culture assays utilizing mouse lymphoma cells and Chinese hamster ovary cells, and in an in vivo micronucleus assay in mice.

Fertility: There are no irreversible effects on fertility following cessation of exposures to levonorgestrel or progestins in general.

14 CLINICAL STUDIES

A double-blind, randomized, multicenter, multinational study evaluated and compared the efficacy and safety of three different regimens for emergency contraception. Subjects were enrolled at 15 sites in 10 countries; the racial/ethnic characteristics of the study population overall were 54% Chinese, 34% Caucasian, and 12% Black or Asian (other than Chinese). 2,381 healthy women with a mean age of 27 years, who needed emergency contraception within 72 hours of unprotected intercourse were involved and randomly allocated into one of the two levonorgestrel groups. A single dose of 1.5 mg of levonorgestrel (Plan B One-Step) was administered to women allocated into group 1. Two doses of 0.75 mg levonorgestrel 12 hours apart (Plan B) were administered to women in group 2. In the Plan B One-Step group, 16 pregnancies occurred in 1,198 women and in the Plan B group, 20 pregnancies occurred in 1,183 women. The number of pregnancies expected in each group was calculated based on the timing of intercourse with regard to each woman’s menstrual cycle. Among women receiving Plan B One-Step, 84% of expected pregnancies were prevented and among those women taking Plan B, 79% of expected pregnancies were prevented. The expected pregnancy rate of 8% (with no contraceptive use) was reduced to approximately 1% with Plan B One-Step.

Emergency contraceptives are not as effective as routine contraception since their failure rate, while low based on a single use, would accumulate over time with repeated use [see INDICATIONS AND USAGE (1)].

In the clinical study, bleeding disturbances were the most common adverse event reported after taking the levonorgestrel-containing regimens. More than half of the women had menses within two days of the expected time; however, 31% of women experienced change in their bleeding pattern during the study period; 4.5% of women had menses more than 7 days after the expected time.

16 HOW SUPPLIED/STORAGE AND HANDLING

The Plan B One-Step (levonorgestrel) tablet 1.5 mg is available in a PVC/aluminum foil blister package. The tablet is almost white, round, and marked G00 on one side.

NDC 21695-973-01 (1 tablet unit of use package)

Store Plan B One-Step at 20º to 25ºC (68º to 77ºF) [see USP Controlled Room Temperature].

17 PATIENT COUNSELING INFORMATION

17.1 Information for Patients

- Take Plan B One-Step as soon as possible and not more than 72 hours after unprotected intercourse or a known or suspected contraceptive failure.
- If you vomit within two hours of taking the tablet, immediately contact your healthcare provider to discuss whether to take another tablet.
- Seek medical attention if you experience severe lower abdominal pain 3 to 5 weeks after taking Plan B One-Step, in order to be evaluated for an ectopic pregnancy.
- After taking Plan B One-Step, consider the possibility of pregnancy if your period is delayed more than one week beyond the date you expected your period.
- Do not use Plan B One-Step as routine contraception.
- Plan B One-Step is not effective in terminating an existing pregnancy.
- Plan B One-Step does not protect against HIV-infection (AIDS) and other sexually transmitted diseases/infections.
- For women younger than age 17 years, Plan B One-Step is available only by prescription.

Mfg. by Gedeon Richter, Ltd., Budapest, Hungary
for Duramed Pharmaceuticals, Inc.
Subsidiary of Barr Pharmaceuticals, Inc.
Pomona, New York 10970
Phone: 1-800-330-1271
Website: www.PlanBOneStep.com

Revised: August 2009
11001524

Relabeled by:

Rebel Distributors Corp

Thousand Oaks, CA 91320

PRINCIPAL DISPLAY PANEL

FOR CLINIC USE ONLY. NOT FOR RESALE.

NDC 21695-973-01

Plan B
One-Step®

(levonorgestrel) tablet, 1.5 mg

Emergency Contraceptive

Reduces the chance of pregnancy after unprotected sex (if a regular birth control method fails or after sex without birth control)

Not for regular birth control.

Rx only for women
younger than age 17

One Tablet

One Dose

•Take as soon as possible within 72 hours (3 days) after unprotected sex. The sooner you take it, the better Plan B One-Step® will work.

1 Tablet Levonorgestrel 1.5mg

•Not for regular birth control.
Plan B One-Step® should be used only in emergencies.

•Does not protect against HIV/AIDS or other STDs.

Drug Facts

Active ingredient Purpose

Levonorgestrel 1.5mg........................Emergency contraceptive

Use reduces chance of pregnancy after unprotected sex

(if a contraceptive failed or if you did not use birth control)

Warnings

Allergy alert: Do not use if you have ever had an allergic reaction to levonorgestrel

Sexually transmitted diseases (STDs) alert: This product does not protect against HIV/AIDS or other STDs

Do not use

■ if you are already pregnant (because it will not work)

■ for regular birth control

When using this product you may have

■ menstrual changes

■ nausea

■ lower stomach (abdominal) pain

■ tiredness

■ headache

■ dizziness

■ breast pain

■ vomiting

Keep out of reach of children. In case of overdose, get medical help or contact a Poison Control center right away.

Directions

■ women 17 years of age or older:

■ take tablet as soon as possible within 72 hours (3 days) after unprotected sex. The sooner you take it the better it will work.

■ if you vomit within 2 hours of taking the medication, call a healthcare professional to find out if you should repeat the dose

■ prescription only for women younger than age 17. If you are younger than age 17, see a healthcare professional.

Other information

■ before using this product read the enclosed consumer information leaflet for complete directions and information

■ this product is not recommended for regular birth control. It does not work as well as most other birth control methods used correctly.

■ this product works mainly by preventing ovulation (egg release). It may also prevent fertilization of a released egg (joining of sperm and egg) or attachment of a fertilized egg to the uterus (implantation).

■ when used correctly every time you have sex, latex condoms greatly reduce, but do not eliminate, the risk of pregnancy and the risk of catching or spreading HIV, the virus that causes AIDS. See condom labeling for additional STD information.

■ tablet is enclosed in a blister seal. Do not use if the blister seal is broken.

■ store at 20-25°C (68-77°F)

Inactive ingredients

colloidal silicon dioxide, corn starch, lactose monohydrate, magnesium stearate, potato starch, talc

Questions or comments?

For more information or to speak to a healthcare professional,

call 1-800-330-1271, 24 hours a day/7 days a week.

Visit our Web site at www.PlanBOneStep.com